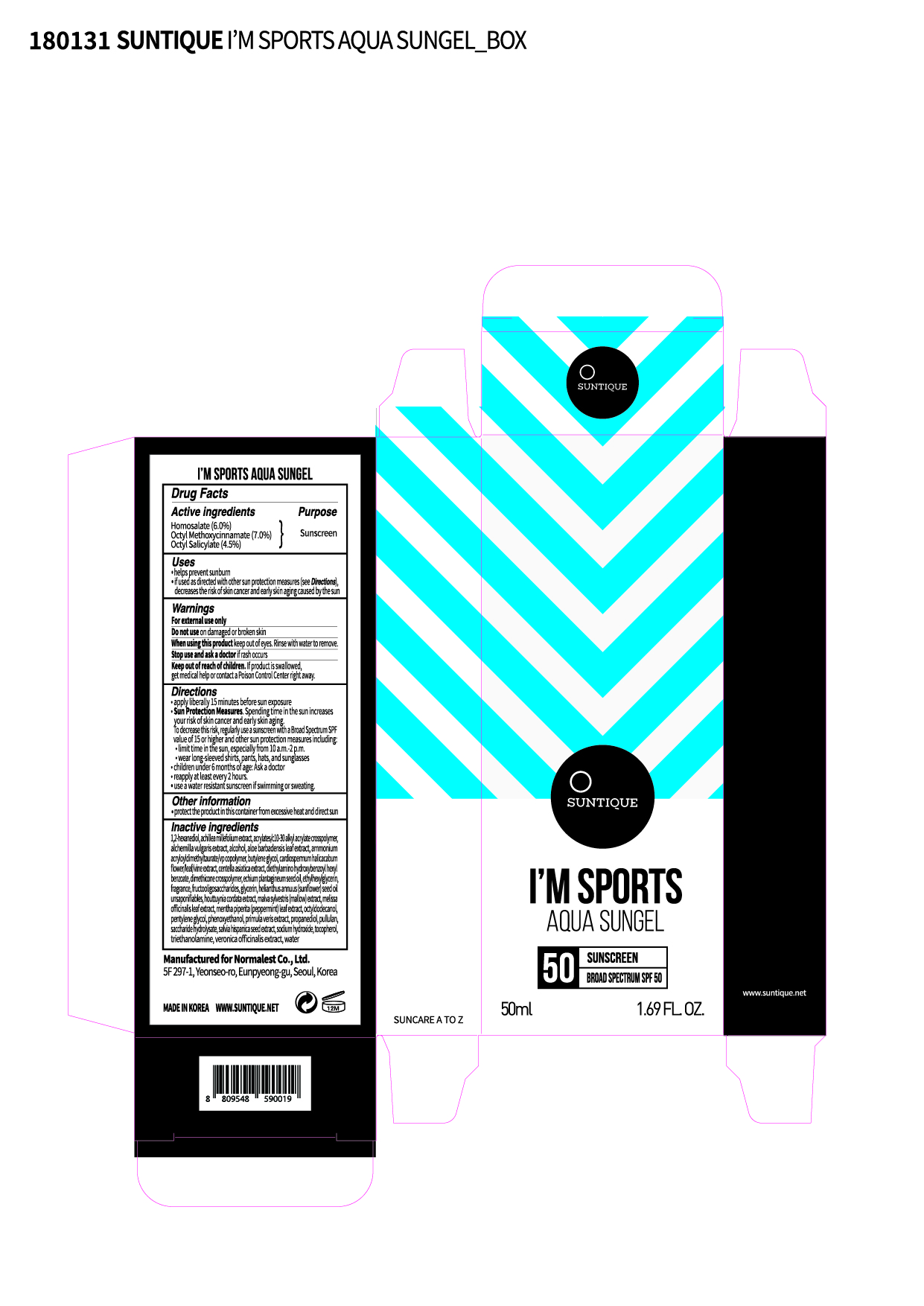 DRUG LABEL: IM SPORTS AQUA SUNGEL
NDC: 72284-0006 | Form: LOTION
Manufacturer: Normalest Co., Ltd.
Category: otc | Type: HUMAN OTC DRUG LABEL
Date: 20190306

ACTIVE INGREDIENTS: OCTINOXATE 3.5 g/50 mL; HOMOSALATE 3 g/50 mL; OCTISALATE 2.25 g/50 mL
INACTIVE INGREDIENTS: DIETHYLAMINO HYDROXYBENZOYL HEXYL BENZOATE; SODIUM HYDROXIDE; PROPANEDIOL; DIMETHICONE CROSSPOLYMER (450000 MPA.S AT 12% IN CYCLOPENTASILOXANE); HOUTTUYNIA CORDATA WHOLE; PENTYLENE GLYCOL; AMMONIUM ACRYLOYLDIMETHYLTAURATE/VP COPOLYMER; SALVIA HISPANICA SEED; CENTELLA ASIATICA; FOSFRUCTOSE; INVERT SUGAR; ETHYLHEXYLGLYCERIN; OCTYLDODECANOL; 1,2-HEXANEDIOL; ECHIUM PLANTAGINEUM SEED OIL; BUTYLENE GLYCOL; MENTHA PIPERITA LEAF; ALOE VERA LEAF; TOCOPHEROL; WATER; PHENOXYETHANOL; PULLULAN; TROLAMINE; GLYCERIN; ALCOHOL; CARDIOSPERMUM HALICACABUM WHOLE; MALVA SYLVESTRIS WHOLE; ACHILLEA MILLEFOLIUM; MELISSA OFFICINALIS LEAF; PRIMULA VERIS; VERONICA OFFICINALIS WHOLE

PACKAGE LABEL

Active ingredients

Octyl Methoxycinnamate 7%

Homosalate 6%

Octyl Salicylate 4.5%

Inactive ingredients

Water, Diethylamino Hydroxybenzoyl Hexyl Benzoate, Propanediol, Dimethicone Crosspolymer, Pentylene Glycol, Ammonium Acryloyldimethyltaurate/VP Copolymer, Salvia Hispanica Seed Extract, Centella Asiatica Extract, Houttuynia Cordata Extract, Phenoxyethanol, Fragrance, Fructooligosaccharides, Saccharide Hydrolysate, Pullulan, Acrylates/C10-30 Alkyl Acrylate, Crosspolymer, Ethylhexylglycerin, Triethanolamine, Octyldodecanol, 1,2-Hexanediol, Echium Plantagineum Seed Oil, Butylene Glycol, Glycerin, Alcohol, Cardiospermum Halicacabum Flower/Leaf/Vine Extract, Helianthus Annuus (Sunflower) Seed Oil Unsaponifiables, Achillea Millefolium Extract, Alchemilla Vulgaris Extract, Malva Sylvestris (Mallow) Extract, Melissa Officinalis Leaf Extract, Mentha Piperita (Peppermint) Leaf Extract, Primula Veris Extract, Veronica Officinalis Extract, Aloe Barbadensis Leaf Extract, Tocopherol, Sodium Hydroxide